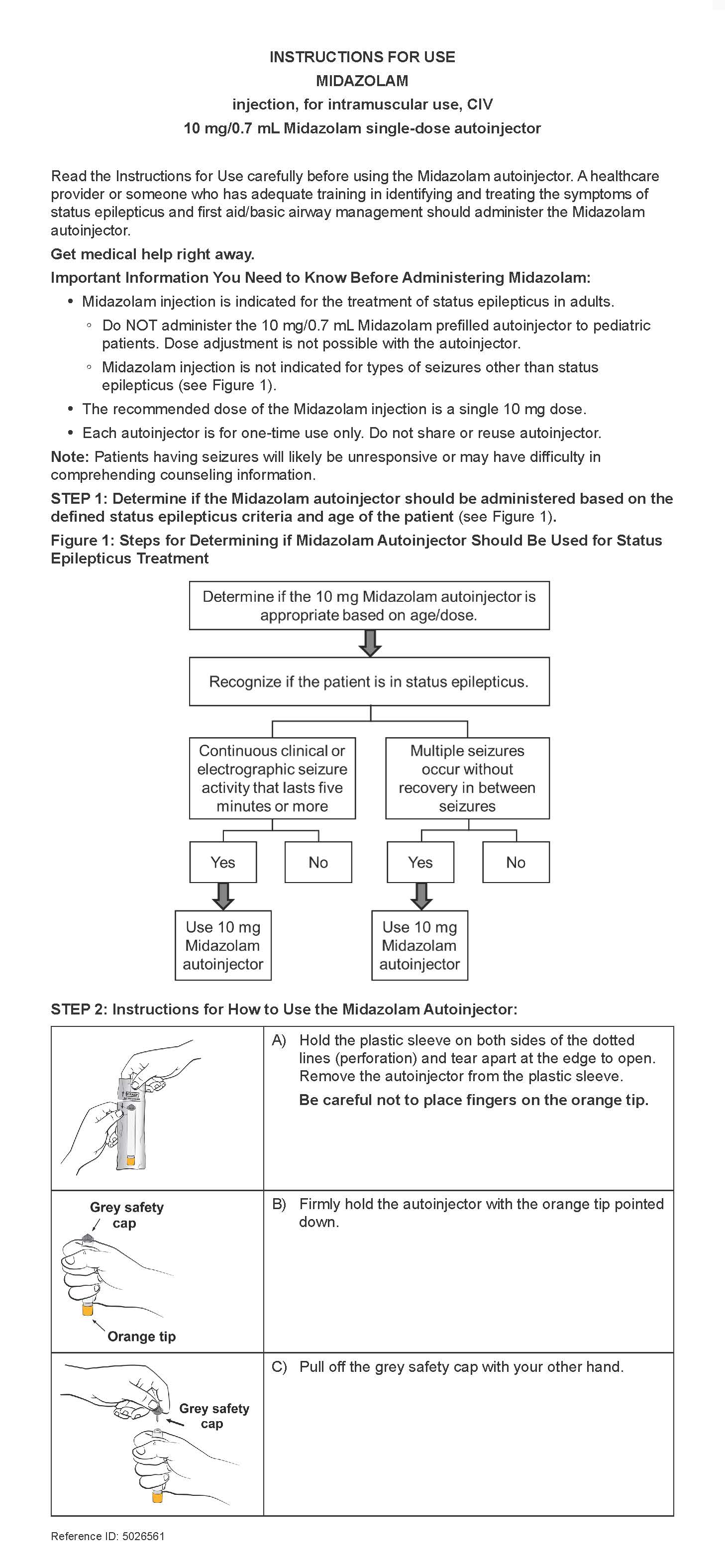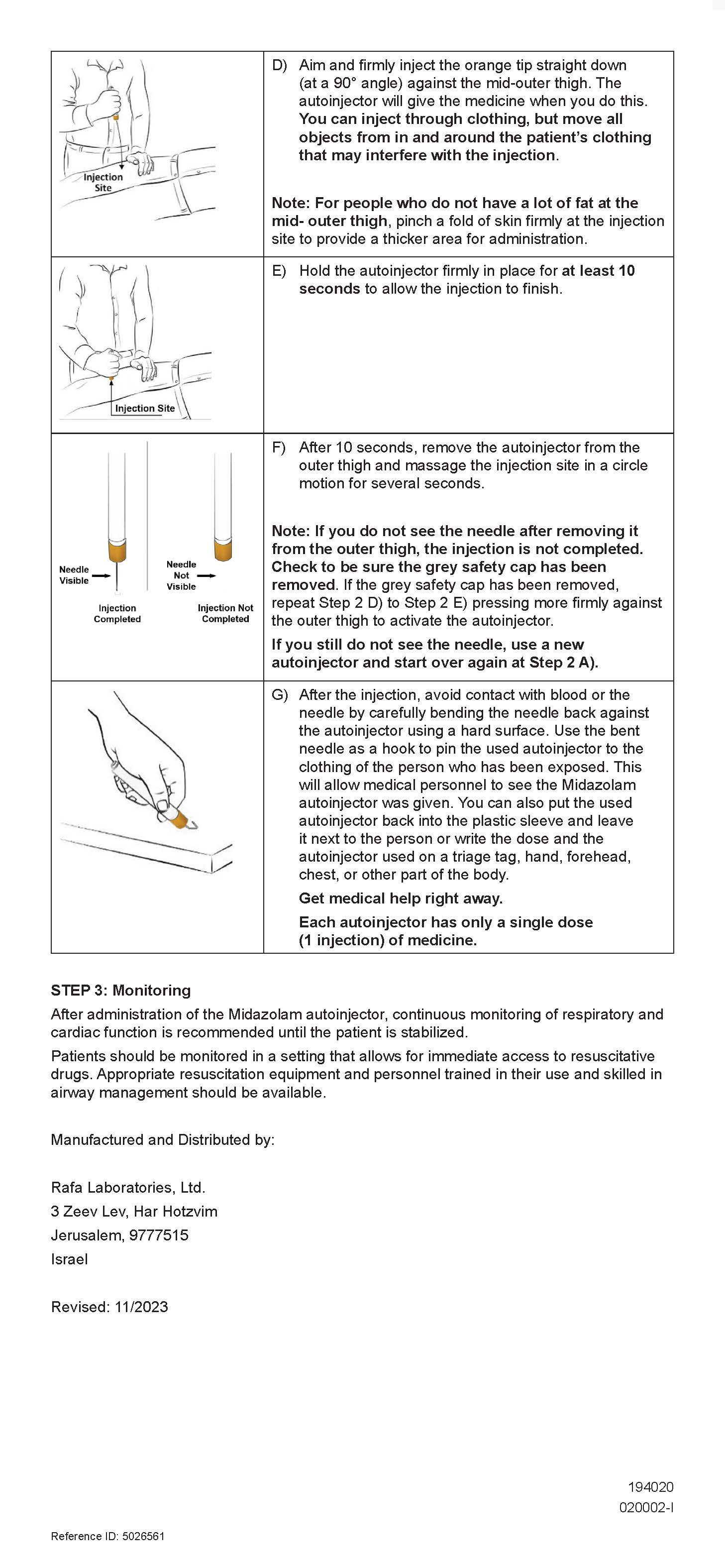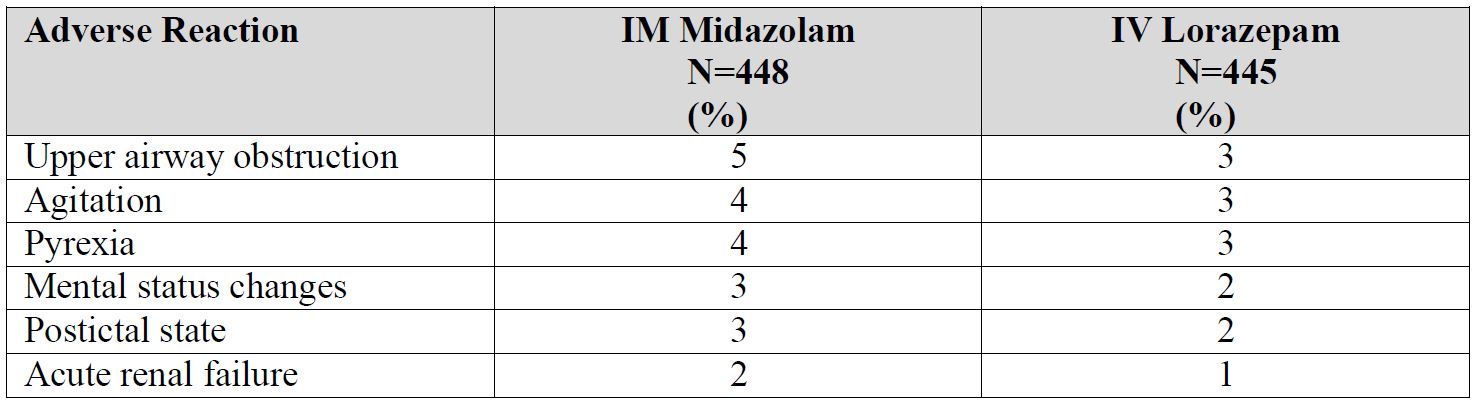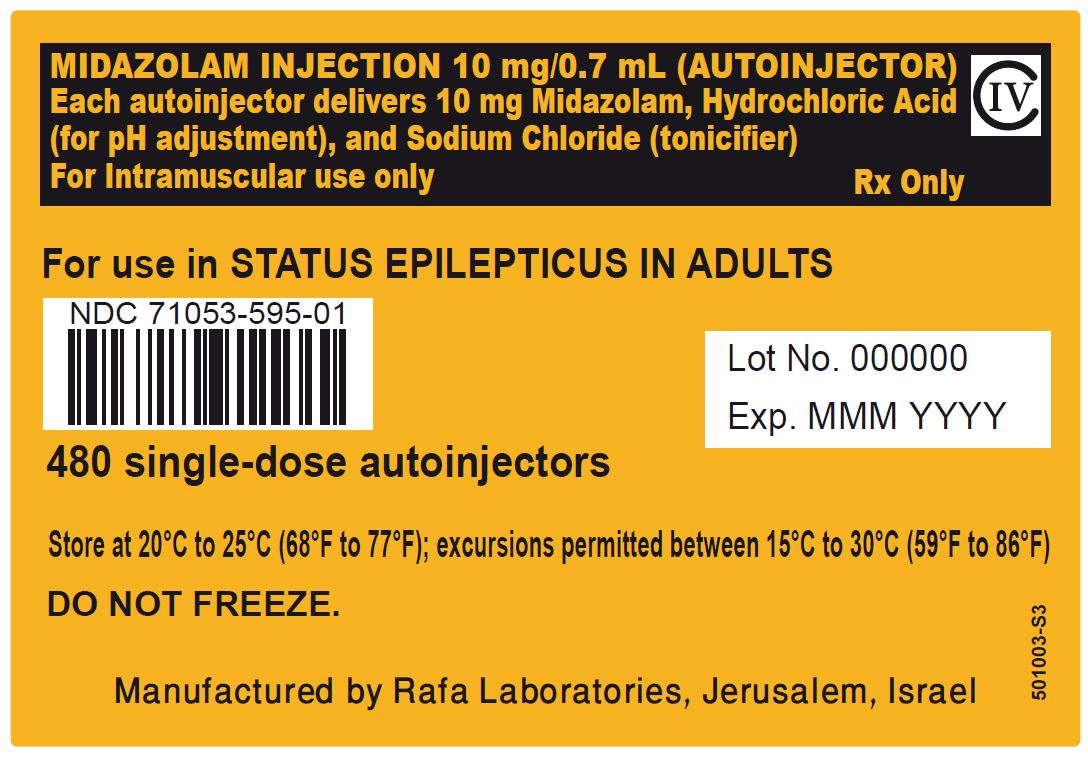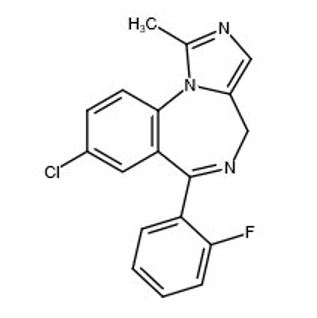 DRUG LABEL: N/A
NDC: 71053-595 | Form: INJECTION, SOLUTION
Manufacturer: Rafa Laboratories, Ltd.
Category: prescription | Type: HUMAN PRESCRIPTION DRUG LABEL
Date: 20260218
DEA Schedule: CIV

ACTIVE INGREDIENTS: MIDAZOLAM 10 mg/0.7 mL

HIGHLIGHTS OF PRESCRIBING INFORMATION

These highlights do not include all the information needed to use MIDAZOLAM INJECTION safely and effectively. See full prescribing information for MIDAZOLAM INJECTION.
MIDAZOLAM injection, for intramuscular use, CIV
Initial U.S. Approval: 1985

INDICATIONS AND USAGE

Midazolam Injection is a benzodiazepine indicated for the treatment of status epilepticus in adults. (1)

DOSAGE AND ADMINISTRATION

- The recommended dose is a single 10 mg dose, administered by intramuscular injection using the prefilled autoinjector. (2.1)
- Inject in the mid-outer thigh (vastus lateralis muscle). (2.2)
- Continuous monitoring of respiratory and cardiac function is recommended. (2.3)

DOSAGE FORMS AND STRENGTHS

Injection: 10 mg/0.7 mL in a single-dose pre-filled autoinjector. (3)

CONTRAINDICATIONS

Hypersensitivity to midazolam. (4)

WARNINGS AND PRECAUTIONS

- Risks of Cardiorespiratory Adverse Reactions: Serious cardiorespiratory adverse reactions have occurred, sometimes resulting in death or permanent neurologic injury, after administration of midazolam. (5.4)
- Other Adverse Reactions: Agitation can occur. (5.5)
- Risks from Concomitant Use of Central Nervous System (CNS) Depressants: May increase risk of hypoventilation, airway obstruction, desaturation, or apnea, and may contribute to profound and/or prolonged drug effect. Practitioners administering Midazolam Injection must have the skills necessary to manage serious cardiorespiratory adverse reactions, including skills in airway management. (5.6)
- Impaired Cognitive Function: Because of partial or complete impairment of recall, patients should not operate hazardous machinery or a motor vehicle until drug effects have subsided. (5.7)
- Glaucoma: Patients with open-angle glaucoma may need to have their ophthalmologic status evaluated following treatment with Midazolam Injection. Midazolam injection is not recommended in patients with narrow-angle glaucoma. (5.8)
- Neonatal Sedation and Withdrawal Syndrome: Midazolam Injection use during pregnancy can result in neonatal sedation and/or neonatal withdrawal.(5.9, 8.1)

ADVERSE REACTIONS

The most common adverse reactions (incidence >3%) in clinical trials in patients with status epilepticus were upper airway obstruction, agitation, and pyrexia. (6.1)
To report SUSPECTED ADVERSE REACTIONS, contact Rafa Laboratories, Ltd. at 1-386-418-7911 or FDA at 1-800-FDA-1088 or
www.fda.gov.medwatch.

DRUG INTERACTIONS

- Benzodiazepines and Opioids: Risk of respiratory depression is increased. (7.1)
- Other CNS Depressants and Alcohol: Sedative effect of midazolam is increased. (7.2)
- Cytochrome P450-3A4 Inhibitors: May result in prolonged sedation due to decreased plasma clearance of midazolam. (7.3)

USE IN SPECIFIC POPULATIONS

Pregnancy: Based on animal data, may cause fetal harm. (8.1)
See 17 for PATIENT COUNSELING INFORMATION.

BOXED WARNING

WARNING: RISKS FROM CONCOMITANT USE WITH OPIOIDS; ABUSE, MISUSE, AND ADDICTION; and DEPENDENCE AND
WITHDRAWAL REACTIONS

See full prescribing information for complete boxed warning.

- Concomitant use of benzodiazepines and opioids may result in profound sedation, respiratory depression, coma, and death. Monitor patients for respiratory depression and sedation. (5.1, 7.1)
- The use of benzodiazepines, including midazolam, exposes users to risks of abuse, misuse, and addiction, which can lead to overdose or death. Before prescribing Midazolam Injection and throughout treatment, assess each patient’s risk for abuse, misuse, and addiction. (5.2)
- Although Midazolam Injection is indicated only for intermittent use (1, 2), if used more frequently than recommended, abrupt discontinuation or rapid dosage reduction of Midazolam Injection may precipitate acute withdrawal reactions, which can be lifethreatening. For patients using Midazolam Injection more frequently than recommended, to reduce the risk of withdrawal reactions, use a gradual taper to discontinue Midazolam Injection. (5.3)

FULL PRESCRIBING INFORMATION

INDICATIONS AND USAGE

Midazolam Injection is indicated for the treatment of status epilepticus in adults.

DOSAGE AND ADMINISTRATION

Recommended Dose
The recommended dose of Midazolam Injection is a single 10 mg dose, administered by intramuscular injection [see Dosage and Administration (2.2)].
Important Administration Instructions

Midazolam Injection should be administered by trained personnel who have had adequate training in the recognition and treatment of status epilepticus and first aid/basic airway management.

Midazolam Injection is for intramuscular use only as a single dose. Inject in the mid-outer thigh (vastus lateralis muscle) using the prefilled autoinjector. The Midazolam autoinjector can inject through clothing. Move all objects from in and around the patient’s clothing that may interfere with the injection. For people who do not have a lot of fat at the mid-outer thigh, bunch up the thigh at the injection site to provide a thicker area for administration.

Parenteral drug products should be inspected visually for particulate matter and discoloration prior to administration, whenever solution and container permit [see Dosage Forms and Strengths (3)].
Refer to the illustrated Midazolam Injection Instructions for Use for autoinjector administration instructions.
Monitoring
After administration of Midazolam Injection, continuous monitoring of respiratory and cardiac function is recommended until the patient is stabilized. Serious and life-threatening cardiorespiratory adverse reactions, such as hypoventilation, airway obstruction, apnea, and hypotension have been reported with the use of midazolam. Patients should be monitored in a setting that allows for immediate access to resuscitative drugs. Appropriate resuscitation equipment and personnel trained in their use and skilled in airway management should be available [see Warnings and Precautions (5.4), Adverse Reactions (6.1)].

Observation for signs of cardiorespiratory depression is particularly important in patients with chronic obstructive pulmonary disease (COPD), patients 60 or more years of age, and patients who have received concomitant narcotics or other central nervous system (CNS) depressants.

DOSAGE FORMS AND STRENGTHS

Injection: 10 mg/0.7 mL of a sterile, clear, colorless to slightly yellow liquid solution in a single-dose prefilled autoinjector.

CONTRAINDICATIONS

Midazolam Injection is contraindicated in patients with a known hypersensitivity to midazolam.

WARNINGS AND PRECAUTIONS

Risks from Concomitant Use with Opioids

Concomitant use of benzodiazepines, including Midazolam Injection, and opioids may result in profound sedation, respiratory depression, coma, and death. If a decision is made to use midazolam concomitantly with opioids, monitor patients closely for respiratory depression and sedation [see Drug Interactions (7.1)].
Trained personnel administering Midazolam Injection must have the skills necessary to manage serious cardiorespiratory adverse reactions, including skills in airway management.

Abuse, Misuse, and Addiction

The use of benzodiazepines, including Midazolam Injection, exposes users to the risks of abuse, misuse, and addiction, which can lead to overdose or death. Abuse and misuse of benzodiazepines often (but not always) involve the use of doses greater than the maximum recommended dosage and commonly involve concomitant use of other medications, alcohol, and/or illicit substances, which is associated with an increased frequency of serious adverse outcomes, including respiratory depression, overdose, or death [see Drug Abuse and Dependence (9.2)].
Before prescribing Midazolam Injection and throughout treatment, assess each patient’s risk for abuse, misuse, and addiction. Use of Midazolam Injection, particularly in patients at elevated risk, necessitates counseling about the risks and proper use of Midazolam Injection along with monitoring for signs and symptoms of abuse, misuse, and addiction. Do not exceed the recommended dosing frequency; avoid or minimize concomitant use of CNS depressants and other substances associated with abuse, misuse, and addiction (e.g., opioid analgesics, stimulants); and advise patients on the proper disposal of unused drug. If a substance use disorder is suspected, evaluate the patient and institute (or refer them for) early treatment, as appropriate.

Dependence and Withdrawal Reactions After Use of Midazolam Injection More Frequently Than Recommended

For patients using Midazolam Injection more frequently than recommended, to reduce the risk of withdrawal reactions, use a gradual taper to discontinue Midazolam Injection (a patient-specific plan should be used to taper the dose).
Patients at an increased risk of withdrawal adverse reactions after benzodiazepine discontinuation or rapid dosage reduction include those who take higher dosages, and those who have had longer durations of use.

Acute Withdrawal Reactions

The continued use of benzodiazepines may lead to clinically significant physical dependence. Although Midazolam Injection is indicated only for intermittent use [see Indications and Usage (1) and Dosage and Administration (2)], if used more frequently than recommended, abrupt discontinuation or rapid dosage reduction of Midazolam Injection, or administration of flumazenil (a benzodiazepine antagonist) may precipitate acute withdrawal reactions, which can be life-threatening (e.g., seizures) [see Drug Abuse and Dependence (9.3)].

Protracted Withdrawal Syndrome

In some cases, benzodiazepine users have developed a protracted withdrawal syndrome with withdrawal symptoms lasting weeks to more than 12 months [see Drug Abuse and Dependence (9.3)].

Risks of Cardiorespiratory Adverse Reactions

Serious cardiorespiratory adverse reactions have occurred after administration of midazolam. These have included respiratory depression, airway obstruction, oxygen desaturation, apnea, respiratory arrest and/or cardiac arrest, sometimes resulting in death or permanent neurologic injury. There have also been rare reports of hypotensive episodes requiring treatment during or after diagnostic or surgical manipulations, particularly in patients with hemodynamic instability. Hypotension occurs more frequently in patients premedicated with a narcotic. The danger of hypoventilation, airway obstruction, or apnea is greater in elderly patients and those with chronic disease states or decreased pulmonary reserve [see Use in Specific Populations (8.5, 8.7)]; patients with COPD are highly sensitive to the respiratory depressant effect of midazolam. Midazolam Injection should be administered with caution to patients in shock or coma with depression of vital signs.
Trained personnel administering Midazolam Injection must have the skills necessary to manage serious cardiorespiratory adverse reactions, including skills in airway management.

Other Adverse Reactions

Reactions such as agitation, involuntary movements (including tonic/clonic movements and muscle tremor), hyperactivity, and combativeness have been reported with midazolam when used for sedation. These reactions may be caused by inadequate or excessive dosing or improper administration of midazolam; however, consideration should be given to the possibility of cerebral hypoxia or true paradoxical reactions. Agitation also occurred in the randomized controlled clinical study of midazolam injection in patients with status epilepticus [see Adverse Reactions (6.1)].

Risks from Concomitant Use of Central Nervous System Depressants

Concomitant use of barbiturates, alcohol or other central nervous system depressants may increase the risk of hypoventilation, airway obstruction, desaturation, or apnea and may contribute to profound and/or prolonged drug effect. Midazolam Injection should be administered with caution to patients in acute alcohol intoxication with depression of vital signs. Narcotic premedication also depresses the ventilatory response to carbon dioxide stimulation.
The efficacy and safety of midazolam in clinical use are functions of the dose administered, the clinical status of the individual patient, and the use of concomitant medications capable of depressing the central nervous system (CNS). Anticipated effects range from mild sedation to deep levels of sedation virtually equivalent to a state of general anesthesia where the patient may require external support of vital functions. Trained personnel administering Midazolam Injection must have the skills necessary to manage serious cardiorespiratory adverse reactions, including skills in airway management. For information regarding withdrawal, see Drug Abuse and Dependence (9.3).

Impaired Cognitive Function

Midazolam is associated with a high incidence of partial or complete impairment of recall for several hours following an administered dose. Gross tests of recovery from the effects of midazolam cannot be relied upon to predict reaction time under stress. It is recommended that no patient operate hazardous machinery or a motor vehicle until the effects of the drug, such as drowsiness, have subsided, and as their medical condition permits.

Glaucoma

Benzodiazepines, including Midazolam Injection, can increase intraocular pressure in patients with glaucoma. Measurements of intraocular pressure in patients without eye disease show a moderate lowering following induction with midazolam; patients with glaucoma have not been studied. Patients with open-angle glaucoma may need to have their ophthalmologic status evaluated following treatment with Midazolam Injection. Midazolam Injection is not recommended in patients with narrow-angle glaucoma.

Neonatal Sedation and Withdrawal Syndrome

Use of Midazolam Injection late in pregnancy can result in sedation (respiratory depression, lethargy, hypotonia) and/or withdrawal symptoms (hyperreflexia, irritability, restlessness, tremors, inconsolable crying, and feeding difficulties) in the neonate [see Use in Specific Populations (8.1)]. Monitor neonates exposed to Midazolam Injection during pregnancy or labor for signs of sedation and monitor neonates exposed to Midazolam Injection during pregnancy for signs of withdrawal; manage these infants accordingly.

ADVERSE REACTIONS

The following serious adverse reactions are discussed in greater detail in other sections:

- Risks from Concomitant Use with Opioids [see Warnings and Precautions (5.1)]
- Abuse, Misuse, and Addiction [see Warnings and Precautions (5.2)]
- Dependence and Withdrawal Reactions After Use of Midazolam Injection More Frequently Than Recommended [see Warnings and Precautions (5.3)]
- Risks of Cardiorespiratory Adverse Reactions [see Warnings and Precautions (5.4)]
- Other Adverse Reactions [see Warnings and Precautions (5.5)]
- Risks from Concomitant Use of Central Nervous System Depressants [see Warnings and Precautions (5.6)]
- Impaired Cognitive Function [see Warnings and Precautions (5.7)]
- Glaucoma [see Warnings and Precautions (5.8)]
- Neonatal Sedation and Withdrawal Syndrome [see Warnings and Precautions (5.9)]

Clinical Trials Experience

Because clinical trials are conducted under widely varying conditions, adverse reaction rates observed in the clinical trials of a drug cannot be directly compared to rates in the clinical trials of another drug and may not reflect the rates observed in practice.
The safety of Midazolam Injection has been established by data from an adequate and well-controlled study of a different midazolam injection in adult patients with status epilepticus [see Clinical Studies (14)]. Below is a display of the adverse reactions of midazolam injection in this adequate and well-controlled study.
Adverse Reactions in the Controlled Study of Intramuscular Midazolam in Patients with Status Epilepticus
In a double-blind, randomized, active-controlled clinical study, 448 patients were assigned to receive intramuscular (IM) midazolam via an autoinjector, and 445 were assigned to receive intravenous (IV) lorazepam. Approximately 45% of patients were female, and the mean age was 43 years. Patients were administered treatment by a healthcare professional (e.g., paramedic) prior to arrival at a hospital.
Table 1 lists the adverse reactions occurring in 2% or more of the IM midazolam-treated patients and at a rate
greater than the IV lorazepam-treated patients.

Table 1 Adverse Reactions in 2% or More of IM Midazolam-Treated Patients and More Frequent than in IV Lorazepam-Treated Patients in Out of Hospital Treatment of Status Epilepticus

Adverse Reactions in Other Midazolam Studies
Midazolam Injection is only indicated for status epilepticus, but for uses other than that for which Midazolam Injection is indicated, fluctuations in vital signs were the most frequently seen findings following parenteral administration of midazolam in adults, and included decreased tidal volume and/or respiratory rate decrease [11% of patients following intramuscular administration], as well as variations in blood pressure and pulse rate. The majority of serious adverse effects, particularly those associated with oxygenation and ventilation, have been reported when midazolam was administered with other medications capable of depressing the CNS. The incidence of such events was higher in patients undergoing procedures involving the airway without the protective effect of an endotracheal tube (e.g., upper endoscopy and dental procedures).
The following additional adverse reactions were reported after intramuscular administration in adults: Headache (1.3%), and local effects at the IM injection site including pain (3.7%), induration (0.5%), redness (0.5%), and muscle stiffness (0.3%).

DRUG INTERACTIONS

Effect of Concomitant Use of Benzodiazepines and Opioids

The concomitant use of benzodiazepines and opioids increases the risk of respiratory depression because of actions at different receptor sites in the CNS that control respiration. Benzodiazepines interact at GABAA sites and opioids interact primarily at mu receptors. When benzodiazepines and opioids are combined, the potential for benzodiazepines to significantly worsen opioid-related respiratory depression exists. Limit dosage and duration of concomitant use of benzodiazepines and opioids. Monitor patients closely for respiratory depression and sedation.

Other CNS Depressants and Alcohol

The sedative effect of Midazolam Injection is accentuated by concomitantly administered medication that depresses the central nervous system, particularly opioids (e.g., morphine, meperidine, and fentanyl), secobarbital, and droperidol, and also by alcohol [see Warnings and Precautions (5.1, 5.4, 5.6)].

Cytochrome P450-3A4 Inhibitors

Caution is advised when Midazolam Injection is administered concomitantly with drugs that are known to inhibit the P450-3A4 enzyme system (e.g., cimetidine, erythromycin, diltiazem, verapamil, ketoconazole, and itraconazole). These drug interactions may result in prolonged sedation caused by a decrease in plasma clearance of midazolam [see Clinical Pharmacology (12.3)].

USE IN SPECIFIC POPULATIONS

Pregnancy

Pregnancy Exposure Registry

There is a pregnancy exposure registry that monitors pregnancy outcomes in women exposed to antiepileptic drugs (AEDs), such as Midazolam Injection, during pregnancy. Healthcare providers are encouraged to recommend that pregnant women who are taking Midazolam Injection during pregnancy enroll in the North American Antiepileptic Drug (NAAED) pregnancy registry by calling 1-888-233-2334 or visiting http://www.aedpregnancyregistry.org/.

Risk Summary

Infants born to mothers using benzodiazepines late in pregnancy have been reported to experience symptoms of sedation and/or neonatal withdrawal [see Warnings and Precautions (5.9) and Clinical Considerations]. Available data from published observational studies of pregnant women exposed to benzodiazepines do not report a clear association with benzodiazepines and major birth defects (see Data).
Administration of midazolam to rats and rabbits during the period of organogenesis or to rats during late pregnancy and throughout lactation at doses greater than those used clinically did not result in adverse effects on development (see Animal Data). Data for other benzodiazepines suggest the possibility of increased neuronal cell death and long-term effects on neurobehavioral and immunological function based on findings in animals following prenatal or early postnatal exposure at clinically relevant doses.
The background risk of major birth defects and miscarriage for the indicated population is unknown. All pregnancies have a background risk of birth defects, loss, or other adverse outcomes. In the U.S. general population, the estimated background risk of major birth defects and miscarriage in clinically recognized pregnancies is 2% to 4% and 15% to 20%, respectively.

Clinical Considerations

Fetal/Neonatal Adverse Reactions

Benzodiazepines cross the placenta and may produce respiratory depression, hypotonia, and sedation in neonates. Monitor neonates exposed to Midazolam Injection during pregnancy or labor for signs of sedation, respiratory depression, hypotonia, and feeding problems. Monitor neonates exposed to Midazolam Injection during pregnancy for signs of withdrawal. Manage these neonates accordingly [see Warnings and Precautions (5.9)].

Data

Human Data

Published data from observational studies on the use of benzodiazepines during pregnancy do not report a clear association with benzodiazepines and major birth defects. Although early studies reported an increased risk of congenital malformations with diazepam and chlordiazepoxide, there was no consistent pattern noted. In addition, the majority of more recent case-control and cohort studies of benzodiazepine use during pregnancy, which were adjusted for confounding exposures to alcohol, tobacco and other medications, have not confirmed these findings.

Animal Data

When midazolam (0, 0.2, 1, or 4 mg/kg/day) was administered intravenously to pregnant rats during the period of organogenesis, no adverse effects on embryofetal development were observed. The highest dose tested, which was associated with minimal evidence of maternal toxicity, is approximately 4 times the recommended human dose (RHD) of 10 mg based on body surface area (mg/m^2).
When midazolam (0, 0.2, 0.6, and 2 mg/kg/day) was administered intravenously to rabbits during the period of organogenesis, no adverse effects on embryofetal development were reported. The high dose, which was not associated with evidence of maternal toxicity, is approximately 4 times the RHD on a mg/m^2basis.
When midazolam (0, 0.2, 1, or 4 mg/kg/day) was administered intravenously to female rats during late gestation and throughout lactation, no clear adverse effects were noted in the offspring. The high dose, which was not associated with evidence of maternal toxicity, is approximately 4 times the RHD on a mg/m^2basis.

In published animal studies, administration of benzodiazepines or other drugs that enhance GABAergic inhibition to neonatal rats has been reported to result in widespread apoptotic neurodegeneration in the developing brain at plasma concentrations relevant for seizure control in humans. The window of vulnerability to these changes in rats (postnatal days 0-14) includes a period of brain development that takes place during the third trimester of pregnancy in humans.

Lactation

Risk Summary

Midazolam is excreted in human milk. There are reports of sedation, poor feeding and poor weight gain in infants exposed to benzodiazepines through breast milk. There are no data on the effects of midazolam on milk production.
The developmental and health benefits of breastfeeding should be considered along with the mother’s clinical need for Midazolam Injection and any potential adverse effects on the breastfed child from Midazolam Injection or from the underlying maternal condition.

Clinical Considerations

Infants exposed to Midazolam Injection through breast milk should be monitored for sedation, poor feeding and poor weight gain.

Pediatric Use

Safety and effectiveness in pediatric patients have not been established. Benzodiazepines are not recognized as a treatment for status epilepticus in neonates and should not be used in this population.

Geriatric Use

Of the total number of patients from the intent-to-treat (ITT) population in the clinical trial of a different midazolam injection, 14.9 percent were 65 years of age and over, while 8.3 percent were 75 years of age and over.
Geriatric patients may have altered drug distribution; diminished hepatic and/or renal function; longer elimination half-lives for midazolam and its metabolites, and subjects over 70 years of age may be particularly sensitive [see Clinical Pharmacology (12.3)]. Administration of IM midazolam to elderly patients has been associated with rare reports of death under circumstances compatible with cardiorespiratory depression [see Warnings and Precautions (5.4)]. In most of these cases, the patients also received other CNS depressants capable of depressing respiration, especially narcotics [see Warnings and Precautions (5.1, 5.6)]. Close
monitoring of geriatric patients is recommended.

Renal Impairment

Patients with renal impairment may have a slower elimination of midazolam and its metabolites, which may result in prolonged drug exposure [see Clinical Pharmacology (12.3)].

Congestive Heart Failure

Patients with congestive heart failure eliminate midazolam more slowly, which may result in prolonged drug exposure [see Clinical Pharmacology (12.3)].

BOXED WARNING

WARNING: RISKS FROM CONCOMITANT USE WITH OPIOIDS; ABUSE, MISUSE, AND ADDICTION; and DEPENDENCE AND WITHDRAWAL REACTIONS

- Concomitant use of benzodiazepines and opioids may result in profound sedation, respiratory depression, coma, and death. Monitor patients for respiratory depression and sedation [see Warnings and Precautions (5.1), Drug Interactions (7.1)].
- The use of benzodiazepines, including midazolam, exposes users to risks of abuse, misuse, and addiction, which can lead to overdose or death. Abuse and misuse of benzodiazepines commonly involve concomitant use of other medications, alcohol, and/or illicit substances, which is associated with an increased frequency of serious adverse outcomes. Before prescribing Midazolam Injection and throughout treatment, assess each patient’s risk for abuse, misuse, and addiction [see Warnings and Precautions (5.2)].
- The continued use of benzodiazepines may lead to clinically significant physical dependence. The risks of dependence and withdrawal increase with longer treatment duration and higher daily dose. Although Midazolam Injection is indicated only for intermittent use [see Indications and Usage (1) and Dosage and Administration (2)], if used more frequently than recommended, abrupt discontinuation or rapid dosage reduction of Midazolam Injection may precipitate acute withdrawal reactions, which can be life-threatening. For patients using Midazolam Injection more frequently than recommended, to reduce the risk of withdrawal reactions, use a gradual taper to discontinue Midazolam Injection [see Warnings and Precautions (5.3)].

OVERDOSAGE

Overdosage of benzodiazepines is characterized by central nervous system depression ranging from drowsiness to coma. In mild to moderate cases, symptoms can include drowsiness, confusion, dysarthria, lethargy, hypnotic state, diminished reflexes, ataxia, and hypotonia. Rarely, paradoxical or disinhibitory reactions (including agitation, irritability, impulsivity, violent behavior, confusion, restlessness, excitement, and talkativeness) may occur. In severe overdosage cases, patients may develop respiratory depression and coma. Overdosage of benzodiazepines in combination with other CNS depressants (including alcohol and opioids) may be fatal [see Warnings and Precautions (5.2)]. Markedly abnormal (lowered or elevated) blood pressure, heart rate, or respiratory rate raise the concern that additional drugs and/or alcohol are involved in the overdosage.

In managing benzodiazepine overdosage, employ general supportive measures, including intravenous fluids and airway maintenance. Flumazenil, a specific benzodiazepine receptor antagonist indicated for the complete or partial reversal of the sedative effects of benzodiazepines in the management of benzodiazepine overdosage, can lead to withdrawal and adverse reactions, including seizures, particularly in the context of mixed overdosage with drugs that increase seizure risk (e.g., tricyclic and tetracyclic antidepressants) and in patients with long-term benzodiazepine use and physical dependency. The risk of withdrawal seizures with flumazenil use may be increased in patients with epilepsy. Flumazenil is contraindicated in patients who have received a benzodiazepine for control of a potentially life-threatening condition (e.g., status epilepticus). If the decision is made to use flumazenil, it should be used as an adjunct to, not as a substitute for, supportive management of benzodiazepine overdosage. See the flumazenil injection Prescribing Information.
Consider contacting a poison center (1-800-221-2222) or a medical toxicologist for additional overdosage management recommendations.

DESCRIPTION

Midazolam is a white to light yellow crystalline compound, insoluble in water. The hydrochloride salt of midazolam, which is formed in situ, is soluble in aqueous solutions. Chemically, midazolam is 8-chloro-6- (2-fluorophenyl)-1-methyl-4H-imidazo[1,5-a][1,4]benzodiazepine. Midazolam has the empirical formula C18H13ClFN3, a calculated molecular weight of 325.77 and the following structural formula:

Midazolam Injection contains a sterile, nonpyrogenic solution for intramuscular injection in a single-dose prefilled autoinjector. Each 0.7 mL contains 10 mg midazolam (equivalent to 11.12 mg midazolam hydrochloride) compounded with 0.7% sodium chloride and 1.1% hydrochloric acid. The pH is adjusted to approximately 3 with hydrochloric acid.

NONCLINICAL TOXICOLOGY

Carcinogenesis, Mutagenesis, Impairment of Fertility

Carcinogenesis

Midazolam maleate was administered in the diet to mice and rats for 2 years at doses of 0, 1, 9, or 80 mg/kg/day. In female mice in the highest dose group there was a marked increase in the incidence of hepatic tumors. In highdose male rats there was a small but statistically significant increase in benign thyroid follicular cell tumors. The highest dose not associated with increased tumor incidences in mice and rats (9 mg/kg/day) is approximately 4 and 9 times, respectively, the recommended human dose (RHD) of 10 mg based on body surface area (mg/m2). The pathogenesis of induction of these tumors is not known. These tumors were found after chronic administration, whereas human use will ordinarily be of single or several doses.

Mutagenesis

Midazolam was negative for genotoxicity in in vitro (Ames, mammalian cell clastogenicity) and in vivo (mouse bone marrow micronucleus) assays.

Impairment of Fertility

When midazolam (0, 1, 4, or 16 mg/kg) was orally administered to male and female rats prior to and during mating and continuing in females throughout gestation and lactation, no adverse effects on male or female fertility were noted. Midazolam plasma exposures (AUC) at the highest dose tested were approximately 6 times that in humans at the RHD.

How Supplied

Midazolam Injection is a clear, colorless to slightly yellow sterile solution available in single-dose prefilled autoinjectors containing 10 mg/0.7 mL.
Midazolam Injection is supplied in the following packaging configurations:

- Carton of 480 prefilled autoinjectors: NDC 71053-595-01

Storage and Handling

Store at 20 ºC to 25 ºC (68 ºF to 77 ºF); excursions permitted between 15 ºC and 30 ºC (59 ºF and 86 ºF) [See USP Controlled Room Temperature]. DO NOT FREEZE.

CLINICAL STUDIES

The effectiveness of Midazolam Injection administered via this autoinjector for the treatment of status epilepticus in adults is based upon an adequate and well-controlled study of a different midazolam injection, which is described below, and a bioavailability study comparing intramuscular administration of 10 mg midazolam using this autoinjector versus midazolam vial in healthy adults.
The safety and effectiveness of midazolam injection for the treatment of status epilepticus was established in a multi-center, randomized, double-blind (double-dummy), active-control trial comparing midazolam administered intramuscularly (IM) via a different autoinjector to lorazepam administered intravenously (IV). Patients meeting the diagnosis of status epilepticus, with continuing convulsive seizure activity after the arrival of paramedics, were eligible for enrollment. The ITT population consisted of 893 patients who were randomized to receive either IM midazolam (n=448) or IV lorazepam (n=445). Following randomization, each patient received study treatments administered by a healthcare professional (e.g., paramedic) prior to arrival at a hospital.
According to the double-dummy design, adult patients received 10 mg IM midazolam followed by IV placebo or received IM placebo followed by 4 mg IV lorazepam. The primary efficacy endpoint was the termination of convulsive seizure activity (without the need for rescue medication) prior to arrival at the emergency department (ED) as determined by the ED attending physician. A statistically significantly higher percentage of midazolam-treated patients met the primary efficacy endpoint, as shown in Table 2.

Table 2: Primary Efficacy Analysis Results: Seizure Termination (without rescue medication)
 | IM Midazolam (n=448) | IV Lorazepam
Treatment success (%) | 73.4 | 63.4
p-valuea | 0.002

a Fischer's exact test

DRUG ABUSE AND DEPENDENCE

Controlled Substance

Midazolam Injection contains midazolam, a Schedule IV controlled substance.

Abuse

Midazolam is a benzodiazepine and a CNS depressant with a potential for abuse and addiction. Abuse is the intentional, non-therapeutic use of a drug, even once, for its desirable psychological or physiological effects. Misuse is the intentional use, for therapeutic purposes, of a drug by an individual in a way other than prescribed by a health care provider or for whom it was not prescribed. Drug addiction is a cluster of behavioral, cognitive, and physiological phenomena that may include a strong desire to take the drug, difficulties in controlling drug use (e.g., continuing drug use despite harmful consequences, giving a higher priority to drug use than other activities and obligations), and possible tolerance or physical dependence. Even taking benzodiazepines as prescribed may put patients at risk for abuse and misuse of their medication. Abuse and misuse of benzodiazepines may lead to addiction.

Abuse and misuse of benzodiazepines often (but not always) involve the use of doses greater than the maximum recommended dosage and commonly involve concomitant use of other medications, alcohol, and/or illicit substances, which is associated with an increased frequency of serious adverse outcomes, including respiratory depression, overdose, or death. Benzodiazepines are often sought by individuals who abuse drugs and other substances, and by individuals with addictive disorders [see Warnings and Precautions (5.2)].The following adverse reactions have occurred with benzodiazepine abuse and/or misuse: abdominal pain, amnesia, anorexia, anxiety, aggression, ataxia, blurred vision, confusion, depression, disinhibition, disorientation, dizziness, euphoria, impaired concentration and memory, indigestion, irritability, muscle pain, slurred speech, tremors, and vertigo.

The following severe adverse reactions have occurred with benzodiazepine abuse and/or misuse: delirium, paranoia, suicidal ideation and behavior, seizures, coma, breathing difficulty, and death. Death is more often associated with polysubstance use (especially benzodiazepines with other CNS depressants such as opioids and alcohol).

Midazolam was actively self-administered in primate models used to assess the positive reinforcing effects of psychoactive drugs. Midazolam produced physical dependence of a mild to moderate intensity in cynomolgus monkeys after 5 to 10 weeks of administration.

Available data concerning the drug abuse and dependence potential of midazolam suggest that its abuse potential is at least equivalent to that of diazepam.

Dependence

Physical Dependence After Use of Midazolam Injection More Frequently Than Recommended

Midazolam Injection may produce physical dependence if used more frequently than recommended. Physical dependence is a state that develops as a result of physiological adaptation in response to repeated drug use, manifested by withdrawal signs and symptoms after abrupt discontinuation or a significant dose reduction of a drug. Although Midazolam Injection is indicated only for intermittent use [see Indications and Usage (1) and Dosage and Administration (2)], if used more frequently than recommended, abrupt discontinuation or rapid dosage reduction or administration of flumazenil, a benzodiazepine antagonist, may precipitate acute withdrawal reactions, including seizures, which can be life-threatening. Patients at an increased risk of withdrawal adverse reactions after benzodiazepine discontinuation or rapid dosage reduction include those who take higher dosages (i.e., higher and/or more frequent doses) and those who have had longer durations of use [see Warnings and Precautions (5.3)].

For patients using Midazolam Injection more frequently than recommended, to reduce the risk of withdrawal reactions, use a gradual taper to discontinue Midazolam Injection [see Warnings and Precautions (5.3)].

Acute Withdrawal Signs and Symptoms

Acute withdrawal signs and symptoms associated with benzodiazepines have included abnormal involuntary movements, anxiety, blurred vision, depersonalization, depression, derealization, dizziness, fatigue, gastrointestinal adverse reactions (e.g., nausea, vomiting, diarrhea, weight loss, decreased appetite), headache, hyperacusis, hypertension, irritability, insomnia, memory impairment, muscle pain and stiffness, panic attacks, photophobia, restlessness, tachycardia, and tremor. More severe acute withdrawal signs and symptoms, including life-threatening reactions, have included catatonia, convulsions, delirium tremens, depression, hallucinations, mania, psychosis, seizures, and suicidality.

Protracted Withdrawal Syndrome

Protracted withdrawal syndrome associated with benzodiazepines is characterized by anxiety, cognitive impairment, depression, insomnia, formication, motor symptoms (e.g., weakness, tremor, muscle twitches), paresthesia, and tinnitus that persists beyond 4 to 6 weeks after initial benzodiazepine withdrawal. Protracted withdrawal symptoms may last weeks to more than 12 months. As a result, there may be difficulty in differentiating withdrawal symptoms from potential re-emergence or continuation of symptoms for which the benzodiazepine was being used.

Tolerance

Tolerance to Midazolam Injection may develop after use more frequently than recommended. Tolerance is a physiological state characterized by a reduced response to a drug after repeated administration (i.e., a higher dose of a drug is required to produce the same effect that was once obtained at a lower dose). Tolerance to the therapeutic effect of benzodiazepines may develop; however, little tolerance develops to the amnestic reactions and other cognitive impairments caused by benzodiazepines.

CLINICAL PHARMACOLOGY

Mechanism of Action

The exact mechanism of action for midazolam in the treatment of status epilepticus is not fully understood, but is thought to involve potentiation of GABAergic neurotransmission resulting from binding at the benzodiazepine site of the GABAA receptor.

Pharmacodynamics

The effects of midazolam on the CNS are dependent on the dose administered, the route of administration, and the presence or absence of other medications.

Pharmacokinetics

The pharmacokinetics of midazolam were evaluated in a single dose-escalation trial in healthy subjects; following IM injection of midazolam at doses ranging from fixed total amounts of 5 mg to 30 mg (one half to three times the recommended dose) or body weight based dose of 0.10 mg/kg to 0.49 mg/kg, the overall median time to maximum plasma concentration (Tmax) was observed at approximately 0.5 hours after administration. The rate and extent of systemic exposure, as assessed by maximum plasma concentration (Cmax) and area under the plasma drug concentration-time curve from time 0 to infinity (AUC0-∞), tended to increase proportionally with increasing dose from 5 mg to 30 mg.

Absorption

Following IM administration of a single 10 mg midazolam dose to healthy subjects via this autoinjector, midazolam was absorbed with median Tmax (range) of 0.5 (0.17 to 1.03) hours; midazolam mean (±SD) Cmax and AUC0-∞were 127 (±47.3) ng/mL and 454 (±134) ng∙hr/mL, respectively.

Distribution

The mean (±SD) apparent volume of distribution (Vz/F) of midazolam following a single IM dose of 10 mg midazolam via this autoinjector was 169 (±61.7) L in healthy subjects.
In humans, midazolam has been shown to cross the placenta and enter into fetal circulation, and has been detected in human milk and CSF [see Use in Specific Populations (8.1, 8.2)].
In adults, midazolam is approximately 97% bound to plasma protein, principally albumin. The 1-hydroxy metabolite is approximately 89% bound to plasma protein

Elimination

Elimination of the parent drug takes place via hepatic metabolism of midazolam to hydroxylated metabolites that are conjugated and excreted in the urine.

Metabolism

In vitro studies with human liver microsomes indicate that the biotransformation of midazolam is mediated by the cytochrome P450-3A4 (CYP3A4). This enzyme is present in gastrointestinal tract mucosa, as well as in the liver. The 1-hydroxy-midazolam (also termed alpha-hydroxymidazolam) metabolite comprises 60% to 70% of the biotransformation products of midazolam, while 4-hydroxy-midazolam constitutes 5% or less. Small amounts of a dihydroxy derivative have also been detected, but not quantified. The principal urinary excretion products are glucuronide conjugates of the hydroxylated derivatives.
Studies of the intravenous administration of 1-hydroxy-midazolam in humans suggest that 1-hydroxymidazolam is at least as potent as the parent compound, and may contribute to the net pharmacologic activity of midazolam. In vitro studies have demonstrated that the affinities of 1- and 4-hydroxy-midazolam for the benzodiazepine receptor are approximately 20% and 7%, respectively, relative to midazolam.

Excretion

Following IM administration of 10 mg midazolam via this autoinjector, mean (±SD) terminal elimination halflife was 5.16 (±1.77) hours and mean (±SD) apparent total body clearance (CL/F) of midazolam was and 23.8 (±6.77) L/hr.
The principal urinary excretion product is 1-hydroxy-midazolam in the form of a glucuronide conjugate; smaller amounts of the glucuronide conjugates of 4-hydroxy- and dihydroxy-midazolam are detected as well. The amount of midazolam excreted unchanged in the urine after a single IV dose is less than 0.5%. Following a single IV infusion in 5 healthy volunteers, 45% to 57% of the dose was excreted in the urine as the 1-hydroxymethyl midazolam conjugate.

Specific Populations

Changes in the pharmacokinetic profile of midazolam due to drug interactions, physiological variables, etc., may result in changes in the plasma concentration-time profile and pharmacological response to midazolam in these patients. For example, patients with acute renal failure (ARF) appear to have a longer elimination half-life for midazolam [see Use in Specific Populations (8.6)]. In other groups, the relationship between prolonged half-life and duration of effect has not been established.

Obesity

In a study comparing normal (n=20) and obese patients (n=20), the mean half-life was greater in the obese group (5.9 versus 2.3 hours). This was due to an increase of approximately 50% in the volume of distribution (Vd) corrected for total body weight. The clearance was not significantly different between groups.

Geriatric Patients

In three parallel-group studies, the pharmacokinetics of midazolam administered IV or IM were compared in young (mean age 29 years, n=52) and healthy elderly subjects (mean age 73 years, n=53). Plasma half-life was approximately 2-fold higher in the elderly. The mean Vd based on total body weight increased consistently between 15% and 100% in the elderly. The mean CL (total clearance) decreased approximately 25% in the elderly in two studies, and was similar to that of the younger patients in the other [see Use in Specific Populations (8.5)].

Male and Female Patients

No meaningful differences in midazolam exposures (Cmaxand AUC) were observed between male and female adults after IM administration.

Patients with Congestive Heart Failure

In patients suffering from congestive heart failure, a 2-fold increase in the elimination half-life, a 25% decrease in the plasma clearance, and a 40% increase in the volume of distribution of midazolam were observed.

Patients with Renal Impairment

Patients with renal impairment may have longer elimination half-lives for midazolam and its metabolites [see Use in Specific Populations (8.6)].
Midazolam and 1-hydroxy-midazolam pharmacokinetics were compared between 6 intensive care unit (ICU) patients who developed acute renal failure (ARF) and a control group of subjects with normal renal function. Midazolam was administered as an IV infusion (5 to 15 mg/hour). Midazolam clearance was reduced (1.9 versus 2.8 mL/min/kg), and the half-life was prolonged (7.6 hours versus 13 hours) in the ARF patients. The renal clearance of the 1-hydroxy-midazolam glucuronide was prolonged in the ARF group (4 versus 136 mL/min), and the half-life was prolonged (12 hours versus >25 hours). Plasma levels accumulated in all ARF patients to about ten times that of the parent drug. The relationship between accumulating metabolite levels and prolonged
sedation is unclear.
In a study of chronic renal failure patients (n=15) receiving a single IV dose of midazolam, there was a 2-fold increase in the clearance and volume of distribution, but the half-life remained unchanged. Metabolite levels were not studied.

Patients with Hepatic Impairment

Midazolam pharmacokinetics were studied after a single IV dose (0.075 mg/kg) was administered to 7 patients with biopsy-proven alcoholic cirrhosis and 8 control patients. The mean half-life of midazolam increased 2.5-fold in the patients with cirrhosis. Clearance was reduced by 50% and Vd increased by 20%. In another study in 21 male patients with cirrhosis, without ascites and with normal kidney function as determined by creatinine clearance, no changes in the pharmacokinetics of midazolam or 1-hydroxy-midazolam were observed when compared to healthy individuals. The clinical significance of these findings is unknown.

Drug Interaction Studies

CYP3A4 Inhibitors

Drugs that inhibit the activity of CYP3A4 may inhibit midazolam clearance and elevate midazolam concentrations [see Drug Interactions (7.3)].

- The effect of single oral doses of 800 mg cimetidine and 300 mg ranitidine on steady-state concentrations of oral midazolam was examined in a randomized crossover study (n=8). Cimetidine increased the mean midazolam steady-state concentration from 57 to 71 ng/mL. Ranitidine increased the mean steady-state concentration to 62 ng/mL. No change in choice reaction time or sedation index was detected after dosing with the H2 receptor antagonists.
- In a placebo-controlled study, erythromycin administered as a 500 mg dose, three times a day, for 1 week (n=6), reduced the clearance of midazolam following a single 0.5 mg/kg IV dose. The half-life was approximately doubled.
- The effects of diltiazem (60 mg three times a day) and verapamil (80 mg three times a day) on the pharmacokinetics and pharmacodynamics of midazolam were investigated in a three-way crossover study (n=9). The half-life of midazolam increased from 5 to 7 hours when midazolam was taken in conjunction with verapamil or diltiazem. No interaction was observed in healthy subjects between midazolam and nifedipine.
- In a placebo-controlled study, where saquinavir or placebo was administered orally as a 1200 mg dose three times a day for 5 days (n=12), a 56% reduction in the clearance of midazolam following a single 0.05 mg/kg IV dose was observed. The half-life was approximately doubled.

CYP3A4 Inducers

Drugs that induce the activity of CYP3A4 may increase midazolam clearance and decrease midazolam concentrations.

PATIENT COUNSELING INFORMATION

Midazolam Injection is intended for administration by trained personnel. See the illustrated Instructions for Use.
Patients having seizures will likely be unresponsive or may have difficulty in comprehending counseling information.

Risks from Concomitant Use with Opioids
Inform patients and caregivers that potentially fatal additive effects may occur if Midazolam Injection is used with opioids and not to use such drugs concomitantly unless supervised by a healthcare provider [see Warnings and Precautions (5.1), Drug Interactions (7.1)].
Abuse, Misuse, and Addiction
Inform patients that the use of Midazolam Injection more frequently than recommended, even at recommended dosages, exposes users to risks of abuse, misuse, and addiction, which can lead to overdose and death, especially when used in combination with other medications (e.g., opioid analgesics), alcohol, and/or illicit substances. Inform patients about the signs and symptoms of benzodiazepine abuse, misuse, and addiction; to seek medical help if they develop these signs and/or symptoms; and on the proper disposal of unused drug [see Warnings and Precautions (5.2) and Drug Abuse and Dependence (9.2)].

Withdrawal Reactions
Inform patients that use of Midazolam Injection more frequently than recommended may lead to clinically significant physical dependence and that abrupt discontinuation or rapid dosage reduction of Midazolam Injection may precipitate acute withdrawal reactions, which can be life-threatening. Inform patients that in some cases, patients taking benzodiazepines have developed a protracted withdrawal syndrome with withdrawal symptoms lasting weeks to more than 12 months [see Warnings and Precautions (5.3) and Drug Abuse and Dependence (9.3)].
Concomitant Medications
Advise patients to inform their healthcare provider about any alcohol consumption and medicine they are now taking, especially blood pressure medication and antibiotics, including drugs they buy without a prescription. Alcohol has an increased effect when consumed with benzodiazepines; therefore, caution should be exercised regarding simultaneous ingestion of alcohol during benzodiazepine treatment [see Warnings and Precautions (5.6), Drug Interactions (7)].

Impaired Cognitive Function
Advise patients not to operate hazardous machinery or a motor vehicle until the effects of the drug, such as drowsiness, have subsided [see Warnings and Precautions (5.7)].

Pregnancy
Advise pregnant females that the use of Midazolam Injection late in pregnancy can result in sedation (respiratory depression, lethargy, hypotonia) and/or withdrawal symptoms (hyperreflexia, irritability, restlessness, tremors, inconsolable crying, and feeding difficulties) in newborns [see Warnings and Precautions (5.9) and Use in Specific Populations (8.1)]. Instruct patients to inform their healthcare provider if they are pregnant Encourage patients to enroll in the North American Antiepileptic Drug Pregnancy Registry if they become pregnant. This registry is collecting information about the safety of antiepileptic drugs during pregnancy [see Use in Specific Populations (8.1)].
Lactation
Counsel patients that midazolam, the active ingredient in Midazolam Injection, is excreted in breast milk. Instruct patients to inform their healthcare provider if they are breastfeeding or intend to breastfeed. Instruct breastfeeding patients who have been administered Midazolam Injection to monitor infants for excessive sedation, poor feeding and poor weight gain, and to seek medical attention if they notice these signs [see Use in Specific Populations (8.2)].

Manufactured and Distributed by:

Rafa Laboratories, Ltd.

3 Zeev Lev, Har Hotzvim,

Jerusalem, 9777515

Israel